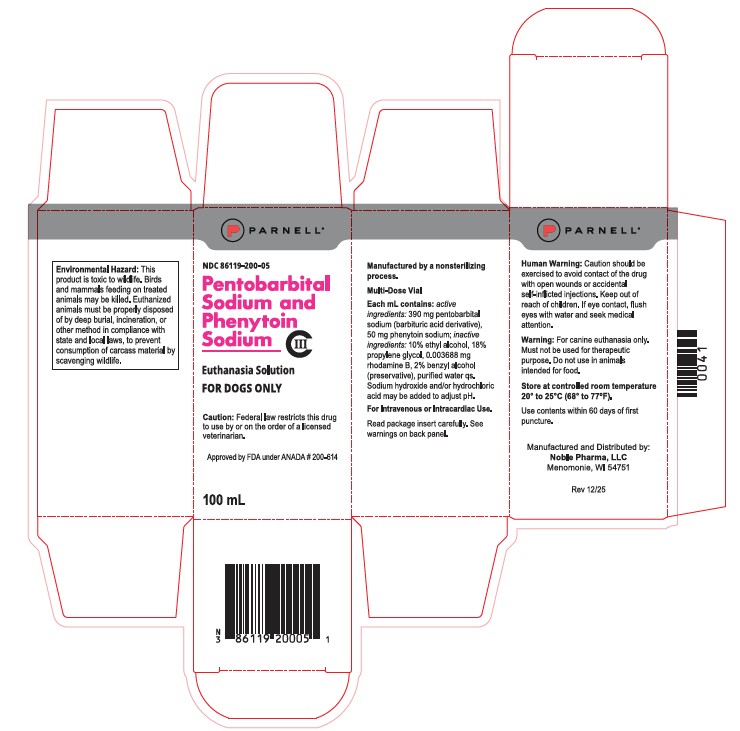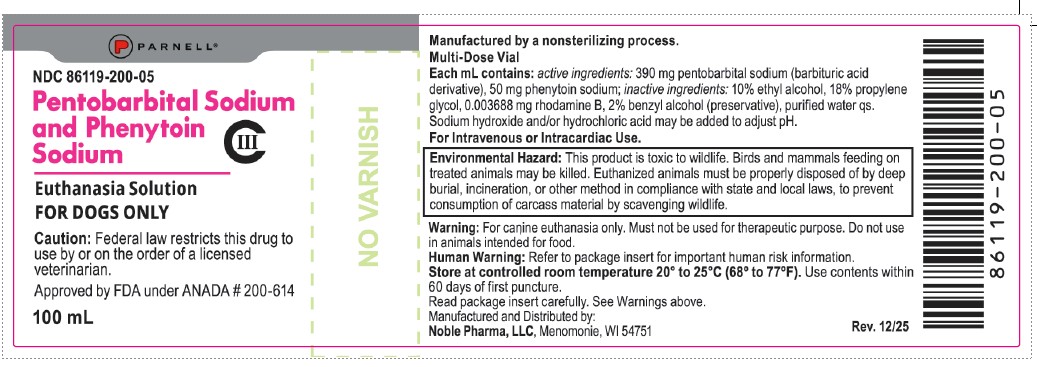 DRUG LABEL: Euthanasia Solution
NDC: 86119-200 | Form: SOLUTION
Manufacturer: Noble Pharma, LLC
Category: animal | Type: PRESCRIPTION ANIMAL DRUG LABEL
Date: 20260209
DEA Schedule: CIII

ACTIVE INGREDIENTS: pentobarbital sodium 390 mg/1 mL; phenytoin sodium 50 mg/1 mL

Euthanasia Solution
Pentobarbital Sodium and Phenytoin Sodium
FOR DOGS ONLY

CAUTION:

Federal law restricts this drug to use by or on the order of a licensed veterinarian.

DESCRIPTION:

A non-sterile solution containing pentobarbital sodium and phenytoin sodium as the active ingredients. Rhodamine B, a bluish-red fluorescent dye, is included in the formulation to help distinguish it from parenteral drugs intended for therapeutic use. Although the solution is not sterile, benzyl alcohol, a bacteriostat, is included to retard the growth of microorganisms.

Each mL contains: Active ingredients: 390 mg pentobarbital sodium (barbituric acid derivative), 50 mg phenytoin sodium; Inactive ingredients: 10% ethyl alcohol, 18% propylene glycol, 0.003688 mg rhodamine B, 2% benzyl alcohol (preservative), water for injection q.s. Sodium hydroxide and/or hydrochloric acid may be added to adjust pH.

ACTIONS:

Euthanasia Solution contains two active ingredients which are chemically compatible but pharmacologically different. Each ingredient acts in such a manner so as to cause humane, painless, and rapid euthanasia. Euthanasia is due to cerebral death in conjunction with respiratory arrest and circulatory collapse. Cerebral death occurs prior to cessation of cardiac activity.

When administered intravenously, pentobarbital sodium produces rapid anesthetic action. There is a smooth and rapid onset of unconsciousness. At the lethal dose, there is depression of vital medullary respiratory and vasomotor centers.

When administered intravenously, phenytoin sodium produces toxic signs of cardiovascular collapse and/or central nervous system depression. Hypotension occurs when the drug is administered rapidly.

Pharmacodynamic Activity: The sequence of events leading to humane, painless, and rapid euthanasia following intravenous injection of Euthanasia Solution is similar to that following intravenous injection of pentobarbital sodium or other barbituric acid derivatives. Within seconds, unconsciousness is induced with simultaneous collapse of the dog. This stage rapidly progresses to deep anesthesia with concomitant reduction in
the blood pressure. A few seconds later, breathing stops, due to depression of the medullary respiratory center; encephalographic activity becomes isoelectric, indicating cerebral death, and then cardiac activity ceases. Phenytoin sodium exerts its effect during the deep anesthesia stage caused by the pentobarbital sodium. This ingredient, due to its cardiotoxic properties, hastens the stoppage of electrical activity in the heart.

INDICATIONS:

For use in dogs for humane, painless, and rapid euthanasia.

WARNING:

For canine euthanasia only. Must not be used for therapeutic purposes. Do not use in animals intended for food.

ENVIRONMENTAL WARNING

ENVIRONMENTAL HAZARD: This product is toxic to wildlife. Birds and mammals feeding on treated animals may be killed. Euthanized animals must be properly disposed of by deep burial, incineration, or other method in compliance with state and local laws, to prevent consumption of carcass material by scavenging wildlife.

HUMAN WARNING:

Caution should be exercised to avoid contact of the drug with open wounds or accidental self-inflicted injections. Keep out of reach of children. If eye contact, flush with water and seek medical advice/attention.

PRECAUTIONS:

Euthanasia may sometimes be delayed in dogs with severe cardiac or circulatory deficiencies. This may be explained by the impaired movement of the drug to its site of action. An occasional dog may elicit reflex responses manifested by motor movement; however, an unconscious animal does not experience pain, because the cerebral cortex is not functioning.

When restraint may cause the dog pain, injury, or anxiety, or danger to the person making the injection, prior use of tranquilizing or immobilizing drugs may be necessary.

Dosage and Administration:

Dosage: Dogs, 1 mL for each 10 pounds of body weight.

Administration: Intravenous injection is preferred. Intracardiac injection may be made when intravenous injection is impractical, as in a very small dog, or in a comatose dog with impaired vascular functions. Good injection skill is necessary for intracardiac injection.

The calculated dose should be given in a single bolus injection.

For intravenous injection, a needle of sufficient gauge to ensure intravenous placement of the entire dose should be used. The use of a Luer-Lok® syringe is recommended to prevent accidental exposure due to needle/syringe separation.

ADVERSE REACTION:

For inquiries or to report suspected adverse drug experiences, please contact Parnell at 1-800-887-2763 or visit www.parnell.com.

For additional information about reporting adverse drug experiences for animal drugs, contact FDA at 1- 888-FDA-VETS or online at www.fda.gov/reportanimalae

To obtain a Safety Data Sheet(s), contact Parnell at 1-800-887-2763 or www.parnell.com

HOW SUPPLIED:

Euthanasia Solution (Pentobarbital Sodium and Phenytoin Sodium) is available in 100 ml multi-dose vials in package of one, NDC 86119-200-05.

STORAGE:

Manufactured by a nonsterilizing process. Store at controlled room temperature 20° to 25°C (68° to 77°F). Use contents within 60 days of first puncture. Approved by FDA under ANADA #200-614

Manufactured and Distributed by:
Noble Pharma, LLC
Menomonie, WI 54751

Rev. 12/25

Luer-Lok is a registered trademark of Becton, Dickinson and Company.